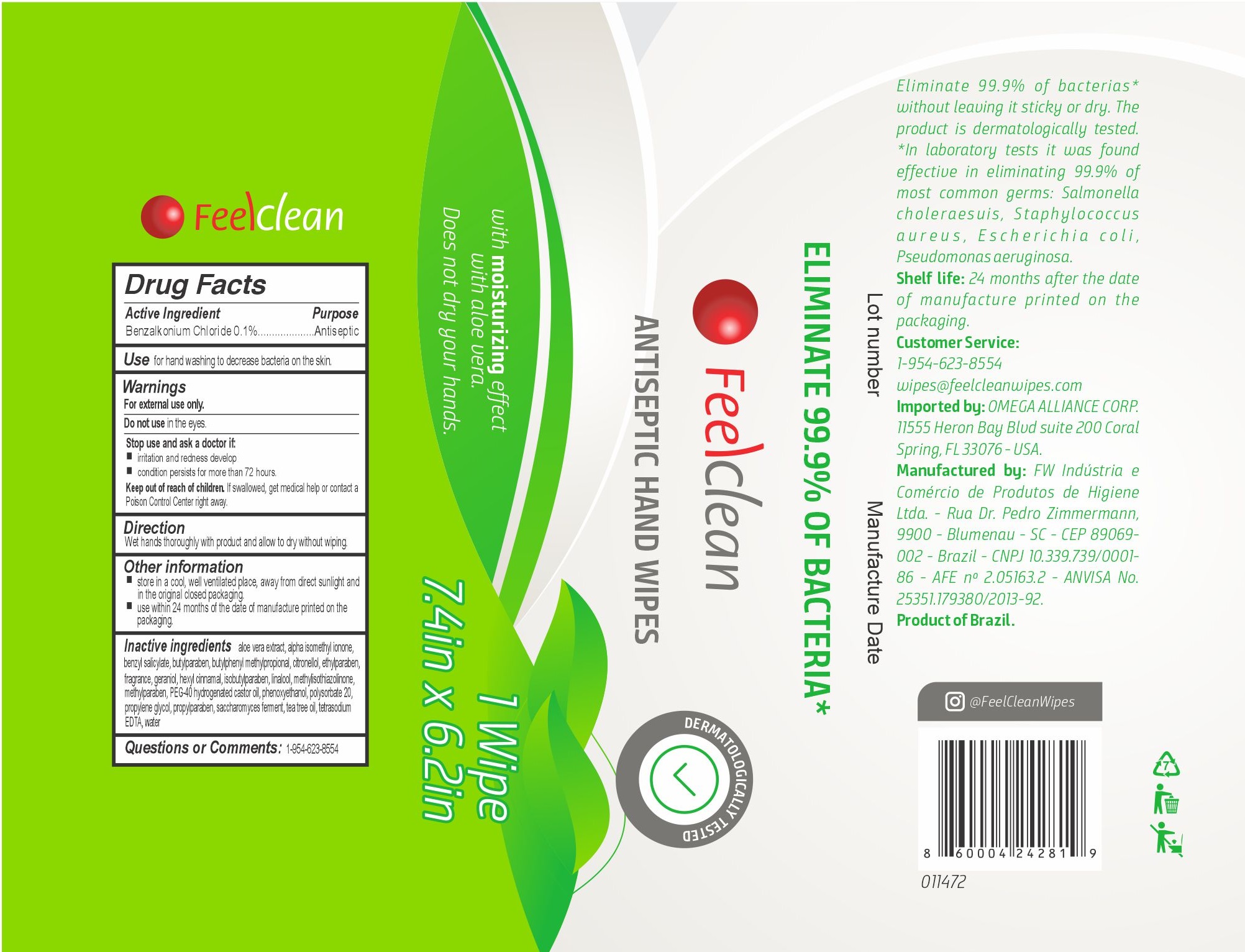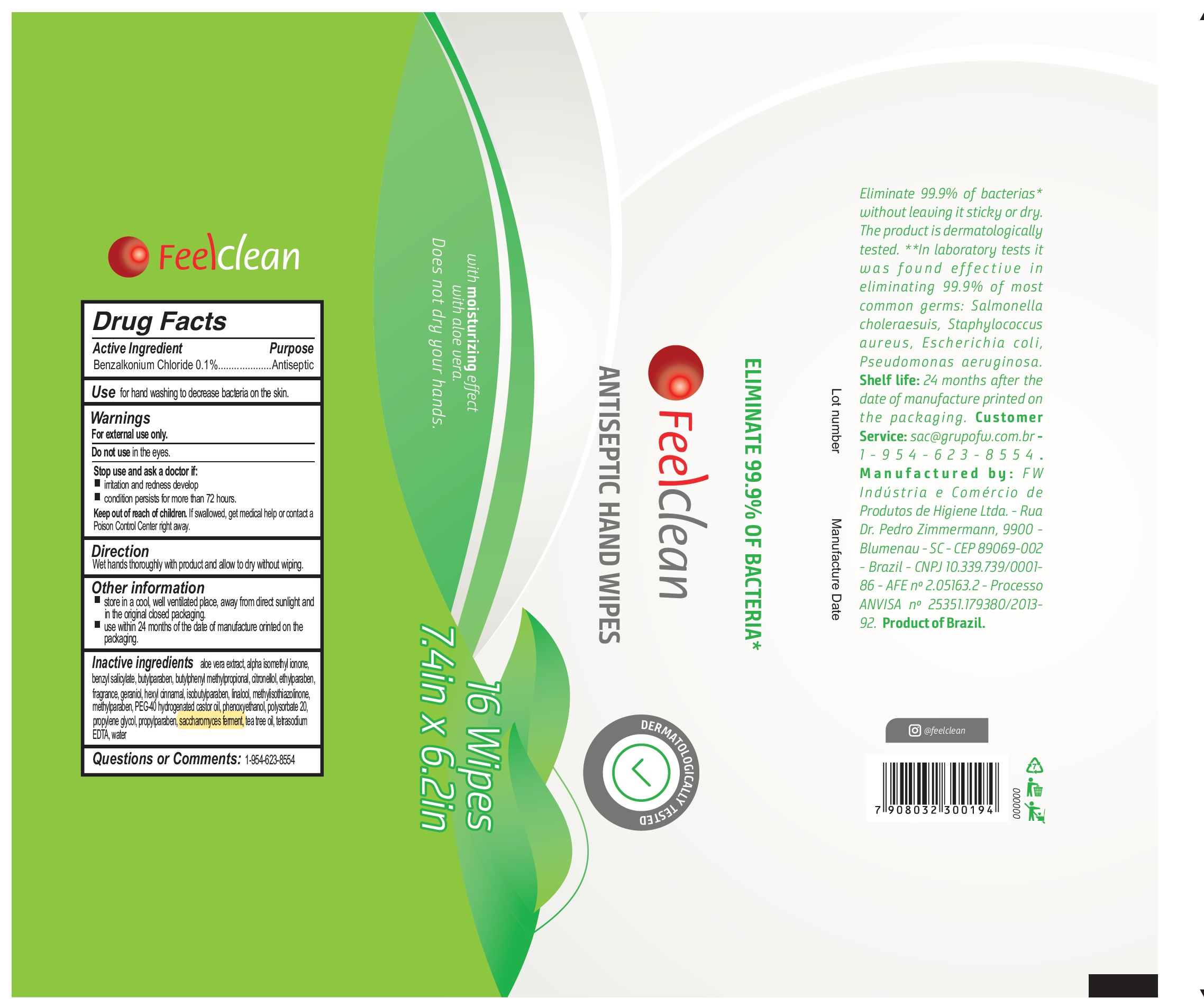 DRUG LABEL: Feel Clean Antiseptic Hand Wipes
NDC: 74883-001 | Form: CLOTH
Manufacturer: FW Industria e Comercio de Produtos de Higiene S A
Category: otc | Type: HUMAN OTC DRUG LABEL
Date: 20220425

ACTIVE INGREDIENTS: BENZALKONIUM CHLORIDE 1 mg/1 mL
INACTIVE INGREDIENTS: ALOE VERA LEAF; ISOMETHYL-.ALPHA.-IONONE; BENZYL SALICYLATE; BUTYLPARABEN; BUTYLPHENYL METHYLPROPIONAL; .BETA.-CITRONELLOL, (R)-; ETHYLPARABEN; GERANIOL; .ALPHA.-HEXYLCINNAMALDEHYDE; ISOBUTYLPARABEN; LINALOOL, (+/-)-; METHYLISOTHIAZOLINONE; METHYLPARABEN; POLYOXYL 40 HYDROGENATED CASTOR OIL; PHENOXYETHANOL; POLYSORBATE 20; PROPYLENE GLYCOL; PROPYLPARABEN; TEA TREE OIL; EDETATE SODIUM; WATER

Feel Clean Antiseptic Hand Wipes

Active Ingredient

Benzalkonium Chloride 0.1%

Purpose

Antiseptic

Use

for hand washing to decrease bacteria on the skin.

Warnings

For external use only.

Do not use

in the eyes.

Stop use and ask a doctor if:

- irritation and redness develop
- condition persists for more than 72 hours.

Keep out of reach of children.

If swallowed, get medical help or contact a Poison Control Center right away.

Direction

Wet hands thoroughly with product and allow to dry without wiping.

Other information

- store in a cool, well ventilated place, away from direct sunlight and in the original closed packaging.
- use within 24 months of the date of manufacture orinted on the packaging

Inactive ingredients

aloe vera extract, alpha isomethyl ionone, benzyl salicylate, butylparaben, butylphenyl methylpropional, citronellol, ethylparaben, fragrance, geraniol, hexyl cinnamal, isobutylparaben, linalool, methylisothiazolinone, methylparaben, PEG-40 hydrogenated castor oil, phenoxyethanol, polysorbate 20, propylene glycol, propylparaben, saccharomyces ferment, tea tree oil, tetrasodium EDTA, water